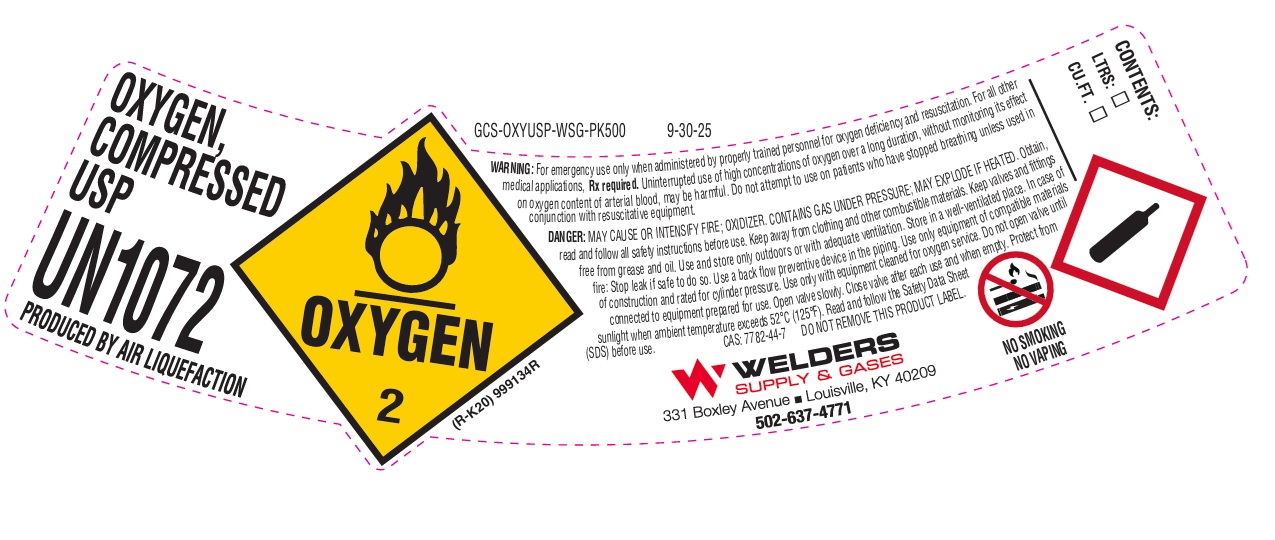 DRUG LABEL: Oxygen
NDC: 84078-002 | Form: GAS
Manufacturer: WELDERS SUPPLY COMPANY OF LOUISVILLE, INC.
Category: prescription | Type: HUMAN PRESCRIPTION DRUG LABEL
Date: 20260128

ACTIVE INGREDIENTS: OXYGEN 992 mL/1 L

Oxygen

PACKAGE LABEL

OXYGEN, COMPRESSED USP

UN1072

PRODUCED BY AIR LIQUEFACTION

WARNING: For emergency use only when administered by properly trained personnel for oxygen deficiency and resuscitation. For all other medical applications, Rx required. Uninterrupted use of high concentrations of oxygen over a long duration, without monitoring its effect on oxygen content of arterial blood, may be harmful. Do not attempt to use on patients who have stopped breathing unless used in conjunction with resuscitative equipment.

DANGER: MAY CAUSE OR INTENSIFY FIRE; OXIDIZER. CONTAINS GAS UNDER PRESSURE; MAY EXPLODE IF HEATED. Obtain, read and follow the safety instructions before use. Keep away from clothing and other combustible materials. Keep valves and fittings free from grease and oil. Use and store only outdoors or with adequate ventilation. Store in a well-ventilated place. In case of fire: Stop leak if safe to do so. Use a back flow preventive device in the piping. Use only equipment of compatible materials of construction and rated for cylinder pressure. Use only with equipment cleaned for oxygen service. Do not open valve until connected to equipment prepared for use. Open valve slowly. Close valve after each use and when empty. Protect from sunlight when ambient temperature exceeds 52 C (125 F). Read and follow the Safety Data Sheet (SDS) before use. CAS: 7782-44-7 DO NOT REMOVE THIS PRODUCT LABEL.

WELDERS SUPPLY & GASES

331 Boxley Avenue Louisville, KY 40209

502-637-4771

NO SMOKING

NO VAPING

CONTENTS:

LTRS:

CU.FT.